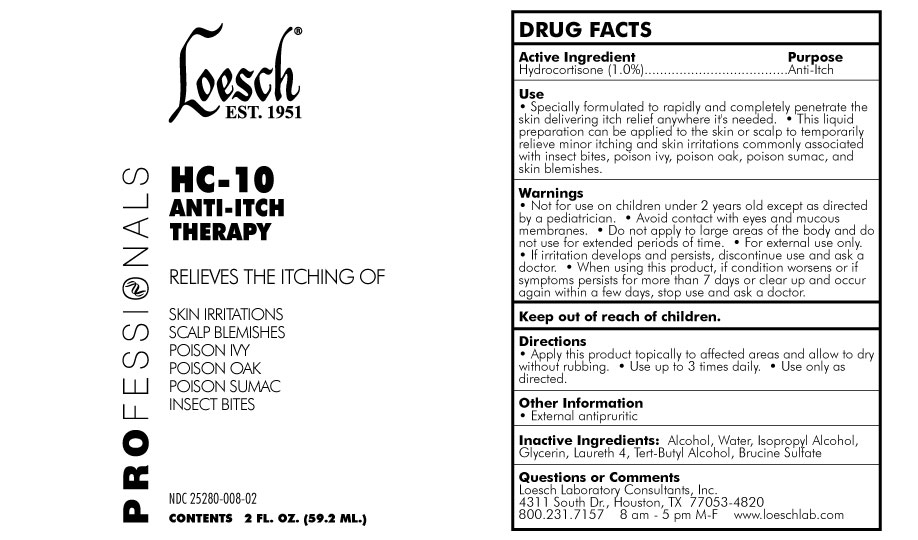 DRUG LABEL: Loesch HC-10 ANTI-ITCH THERAPY
NDC: 25280-008 | Form: LIQUID
Manufacturer: Loesch Laboratory Consultants, INC.
Category: otc | Type: HUMAN OTC DRUG LABEL
Date: 20171101

ACTIVE INGREDIENTS: HYDROCORTISONE 9 mg/1 mL
INACTIVE INGREDIENTS: Alcohol; Isopropyl Alcohol; Water; Glycerin; Laureth-4; Tert-Butyl Alcohol; Brucine Sulfate

Active Ingredient

Hydrocortisone

Purpose

Anti-Itch

Use

•Specially formulated to rapidly and completely penetrate the skin delivering itch relief anywhere it's needed. •This liquid preparation can be applied to the skin or scalp to temporarily relieve minor itching and skin irritations commonly associated with insect bites, poison ivy, poison oak, poison sumac, and skin blemishes.

Warnings

•Not for use on children under 2 years old except as directed by a pediatrician. •Avoid contact with eyes and mucous membranes. •Do not apply to large areas of the body and do not use for extended periods of time. •For external use only. •If irritation develops and persists, discontinue use and ask a doctor. •When using this product, if condition worsens or if symptoms persists for more than 7 days or clear up and occur again within a few days, stop use and ask a doctor.

Keep out of reach of children

Directions

•Apply this product topically to affected areas and allow to dry without rubbing. •Use up to 3 times daily. •Use only as directed.

Other information

• External antipruritic

Inactive Ingredients

•Alcohol, Water, Isopropyl Alcohol, Glycerin, Laureth 4, Tert-Butyl Alcohol, Brucine Sulfate.

Questions or Comments

Loesch Laboratory Consultants, Inc.
4311 South Dr., Houston, TX 77053-4820
800.231.7157
8 am - 5 pm M-F
www.loeschlab.com
Questions or Comments

PACKAGE LABEL

Loesch EST.1951
PROFESSIONALS
HC-10 ANTI-ITCH THERAPY
RELIEVES THE ITCHING OF
SKIN IRRITATIONS
SCALP BLEMISHES
POISION IVY
POISON OAK
POISON SUMAC
INSECT BITES
NDC 25280-008-02
CONTENTS 2 FL. OZ. (59.2 ML.)